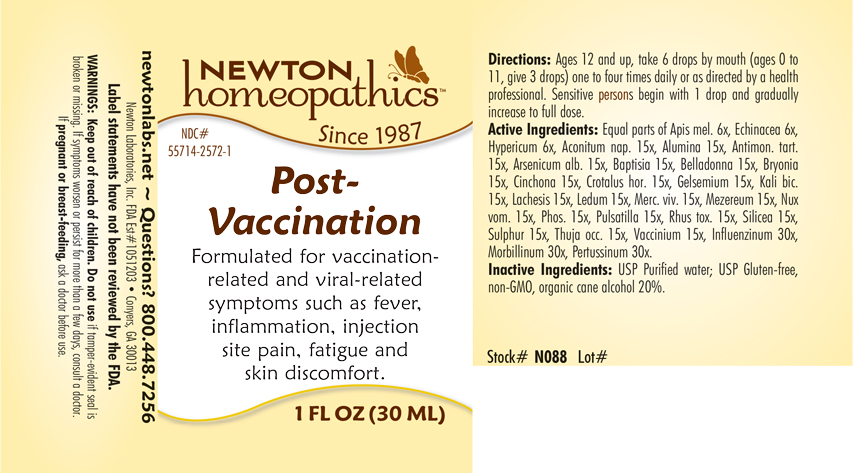 DRUG LABEL: Post - Vaccination
NDC: 55714-2572 | Form: LIQUID
Manufacturer: Newton Laboratories, Inc.
Category: homeopathic | Type: HUMAN OTC DRUG LABEL
Date: 20210706

ACTIVE INGREDIENTS: INFLUENZA A VIRUS 30 [hp_X]/1 mL; INFLUENZA B VIRUS 30 [hp_X]/1 mL; MEASLES VIRUS 30 [hp_X]/1 mL; HUMAN SPUTUM, BORDETELLA PERTUSSIS INFECTED 30 [hp_X]/1 mL; ACONITUM NAPELLUS 15 [hp_X]/1 mL; ALUMINUM OXIDE 15 [hp_X]/1 mL; ANTIMONY POTASSIUM TARTRATE 15 [hp_X]/1 mL; ARSENIC TRIOXIDE 15 [hp_X]/1 mL; BAPTISIA TINCTORIA ROOT 15 [hp_X]/1 mL; ATROPA BELLADONNA 15 [hp_X]/1 mL; BRYONIA ALBA ROOT 15 [hp_X]/1 mL; CINCHONA OFFICINALIS BARK 15 [hp_X]/1 mL; CROTALUS HORRIDUS HORRIDUS VENOM 15 [hp_X]/1 mL; GELSEMIUM SEMPERVIRENS ROOT 15 [hp_X]/1 mL; POTASSIUM DICHROMATE 15 [hp_X]/1 mL; LACHESIS MUTA VENOM 15 [hp_X]/1 mL; LEDUM PALUSTRE TWIG 15 [hp_X]/1 mL; MERCURY 15 [hp_X]/1 mL; DAPHNE MEZEREUM BARK 15 [hp_X]/1 mL; STRYCHNOS NUX-VOMICA SEED 15 [hp_X]/1 mL; PHOSPHORUS 15 [hp_X]/1 mL; PULSATILLA VULGARIS 15 [hp_X]/1 mL; TOXICODENDRON PUBESCENS LEAF 15 [hp_X]/1 mL; SILICON DIOXIDE 15 [hp_X]/1 mL; SULFUR 15 [hp_X]/1 mL; THUJA OCCIDENTALIS LEAFY TWIG 15 [hp_X]/1 mL; BILBERRY 15 [hp_X]/1 mL; APIS MELLIFERA 6 [hp_X]/1 mL; ECHINACEA, UNSPECIFIED 6 [hp_X]/1 mL; HYPERICUM PERFORATUM 6 [hp_X]/1 mL
INACTIVE INGREDIENTS: ALCOHOL; WATER

Post Vac 2572L

OTC - KEEP OUT OF REACH OF CHILDREN SECTION

Keep out of reach of children.

OTC - PREGNANCY OR BREAST FEEDING SECTION

If pregnant or breast-feeding, ask a doctor before use.

WARNINGS SECTION

Warning:Keep out of reach of children. Do no use if tamper-evident seal is broken or missing. If symptoms worsen or persist for more than a few days, consult a doctor. If pregnant or breast-feeding, ask a doctor before use.

QUESTIONS SECTION

newtonlabs.net - Questions? 1.800.448.7256 Newton Laboratories, Inc. FDA Ext # 1051203 - Conyers, GA 30013

INACTIVE INGREDIENT SECTION

Inactive Ingredients: USP Purified Water; USP Gluten-free, non-GMO, organic cane alcohol 20%.

OTC - PURPOSE SECTION

Formulated for vaccination-related and viral-related symptoms such as fever, inflammation, injection site pain, fatigue and skin discomfort.

OTC - ACTIVE INGREDIENT SECTION

Equal parts of Apis mel. 6x, Echinacea 6, Hypericum 6x, Aconitum nap. 15x, Alumina 15x, Antimon. tart.15x, Baptisia 15x, Bryonia 15x, Cinchona 15x, Crotalus horridus 15x, Gelsemium 15x, Kali bic. 15x, Lachesis 15x, Ledum 15x, Merc. viv. 15x, Mezereum 15x, Phosphorus 15x, Pulsatilla 15x, Rhus toxicodendron 15x, Silicea 15x, Sulphur 15x, Thuja occ. 15x, Vaccinium 15x, Arsenicum alb. 15x, Belladonna 15x, Nux vom. 15x, Influenzinum 30x, Morbillinum 30x, Pertussinum 30x.

DOSAGE & ADMINISTRATION SECTION

Ages 12 and up, take 6 drops by mouth (ages 0 to 11, give 3 drops) one to four times daily or as directed by a health professional. Sensitive persons begin with 1 drop and gradually increase to full dose.

INDICATIONS & USAGE SECTION

Formulated for vaccination-related and viral-related symptoms such as fever, inflammation, injection site pain, fatigue and skin discomfort.